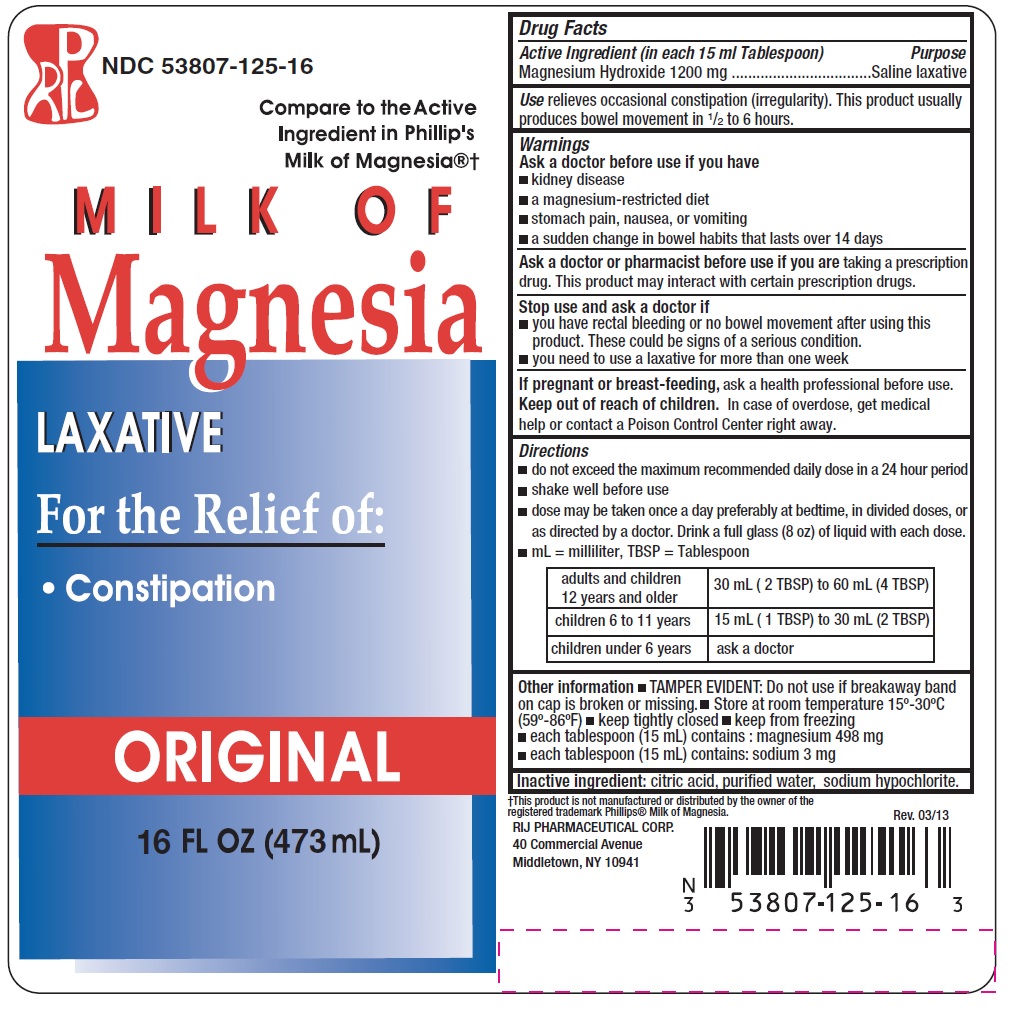 DRUG LABEL: Milk of Magnesia
NDC: 53807-125 | Form: LIQUID
Manufacturer: RIJ Pharmaceutical Corporation
Category: otc | Type: HUMAN OTC DRUG LABEL
Date: 20180430

ACTIVE INGREDIENTS: MAGNESIUM HYDROXIDE 1200 mg/15 mL
INACTIVE INGREDIENTS: CITRIC ACID MONOHYDRATE; WATER; SODIUM HYPOCHLORITE

Drug Facts

Active Ingredient (in each 15 mL Tablespoon)

Magnesium Hydroxide 1200 mg

Purpose

Saline laxative

Use

- relieves occasional constipation (irregularity).
- This product generally produces bowel movement in ½ to 6 hours.

Warnings

Ask a doctor before use if you have

- kidney disease
- a magnesium-restricted diet
- stomach pain, nausea, or vomiting
- a sudden change in bowel habits that lasts more than 14 days

Ask a doctor or pharmacist before use if you are

taking a prescription drug. This product may interact with certain prescription drugs.

Stop use and ask a doctor if

- you have rectal bleeding or no bowel movement after using this product. These could be signs of a serious condition.
- you need to use a laxative for more than one week

If pregnant or breast-feeding,

ask a health professional before use.

Keep out of reach of children.

In case of overdose, get medical help or contact a Poison Control Center right away.

Directions

- do not exceed the maximum recommended daily dose in a 24 hour period
- shake well before use
- dose may be taken once a day preferably at bedtime, in divided doses, or as directed by a doctor. Drink a full glass (8 oz) of liquid with each dose
- mL = milliliter, TBSP = Tablespoonful

adults and children 12 years and older | 30 mL (2 TBSP) to 60 mL (4 TBSP)
children 6 to 11 years | 15 mL (1 TBSP) to 30 mL (2 TBSP)
children under 6 years | ask a doctor

Other information

- TAMPER EVIDENT: Do not use if breakaway band on cap is broken or missing.
- Store at room temperature 15º - 30ºC (59º - 86ºF)
- keep tightly closed
- keep from freezing
- each tablespoon (15 mL) contains: magnesium 498 mg
- each tablespoon (15 mL) contains: sodium 3 mg

Inactive ingredients

citric acid, purified water, sodium hypochlorite